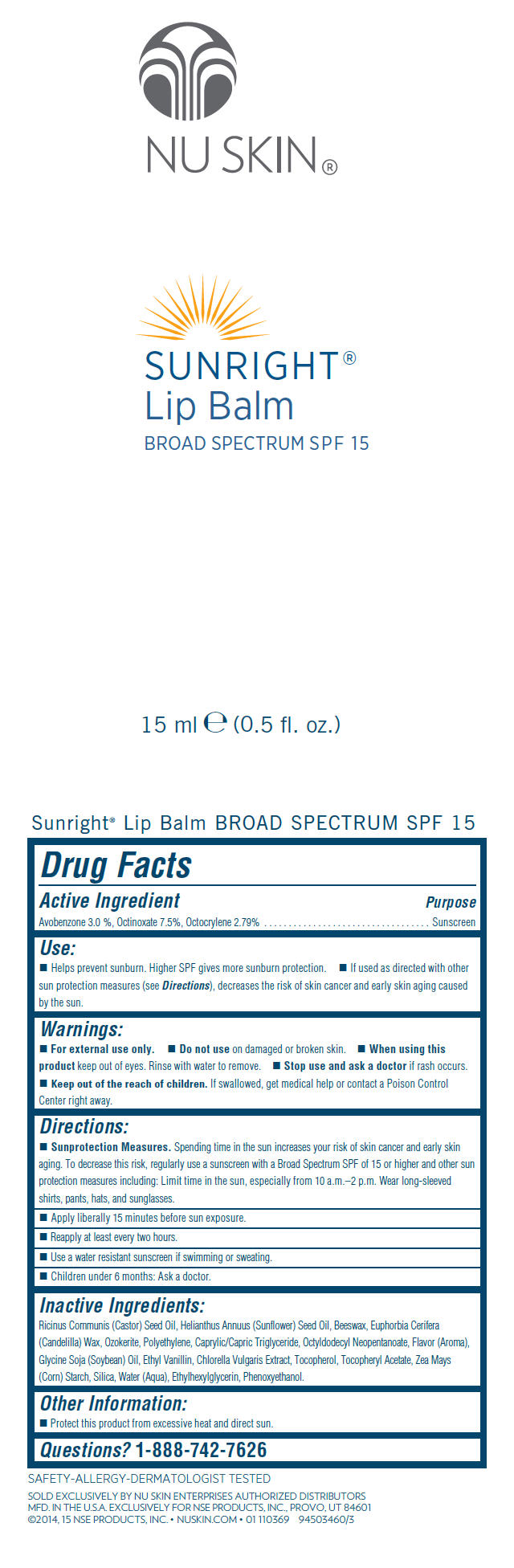 DRUG LABEL: Nu Skin Sunright Lip Balm Broad Spectrum SPF 15
NDC: 62839-6201 | Form: STICK
Manufacturer: NSE Products, Inc.
Category: otc | Type: HUMAN OTC DRUG LABEL
Date: 20220114

ACTIVE INGREDIENTS: Octinoxate 75 mg/1 mL; Avobenzone 30 mg/1 mL; Octocrylene 27.9 mg/1 mL
INACTIVE INGREDIENTS: CASTOR OIL; SUNFLOWER OIL; CANDELILLA WAX; YELLOW WAX; CERESIN; HIGH DENSITY POLYETHYLENE; MEDIUM-CHAIN TRIGLYCERIDES; OCTYLDODECYL NEOPENTANOATE; SOYBEAN OIL; ETHYL VANILLIN; PHENOXYETHANOL; STARCH, CORN; SILICON DIOXIDE; .ALPHA.-TOCOPHEROL ACETATE; TOCOPHEROL; ETHYLHEXYLGLYCERIN; WATER; CHLORELLA VULGARIS

Nu Skin® Sunright® Lip Balm Broad Spectrum SPF 15

Drug Facts

Active Ingredient

Avobenzone 3.0 %, Octinoxate 7.5%, Octocrylene 2.79%

Purpose

Sunscreen

Use

- Helps prevent sunburn. Higher SPF gives more sunburn protection.
- If used as directed with other sun protection measures (see Directions), decreases the risk of skin cancer and early skin aging caused by the sun.

Warnings

- For external use only.

- Do not use on damaged or broken skin.

- When using this product keep out of eyes. Rinse with water to remove.

- Stop use and ask a doctor if rash occurs.

KEEP OUT OF REACH OF CHILDREN

- Keep out of the reach of children. If swallowed, get medical help or contact a Poison Control Center right away.

Directions

- Sunprotection Measures. Spending time in the sun increases your risk of skin cancer and early skin aging. To decrease this risk, regularly use a sunscreen with a Broad Spectrum SPF of 15 or higher and other sun protection measures including: Limit time in the sun, especially from 10 a.m.–2 p.m. Wear long-sleeved shirts, pants, hats, and sunglasses.
- Apply liberally 15 minutes before sun exposure.
- Reapply at least every two hours.
- Use a water resistant sunscreen if swimming or sweating.
- Children under 6 months: Ask a doctor.

Inactive Ingredients

Ricinus Communis (Castor) Seed Oil, Helianthus Annuus (Sunflower) Seed Oil, Beeswax, Euphorbia Cerifera (Candelilla) Wax, Ozokerite, Polyethylene, Caprylic/Capric Triglyceride, Octyldodecyl Neopentanoate, Flavor (Aroma), Glycine Soja (Soybean) Oil, Ethyl Vanillin, Chlorella Vulgaris Extract, Tocopherol, Tocopheryl Acetate, Zea Mays (Corn) Starch, Silica, Water (Aqua), Ethylhexylglycerin, Phenoxyethanol.

Other Information

- Protect this product from excessive heat and direct sun.

Questions?

1-888-742-7626

PRINCIPAL DISPLAY PANEL - 15 ml Tube Pouch Label

NU SKIN®

SUNRIGHT®
Lip Balm
BROAD SPECTRUM SPF 15

15 ml e (0.5 fl. oz.)